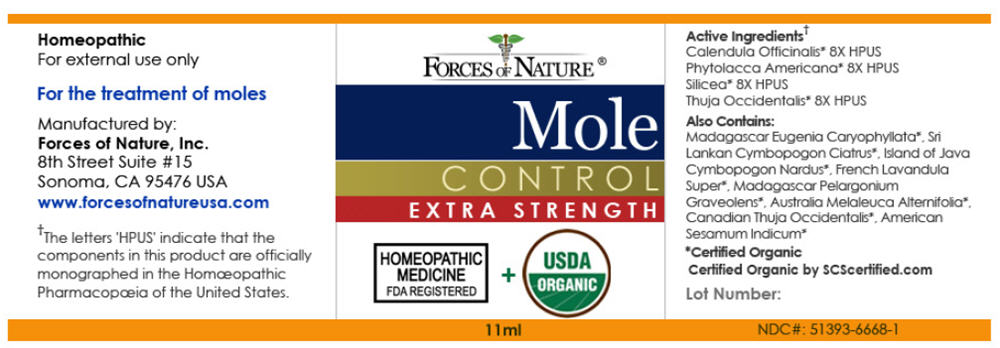 DRUG LABEL: Nevi (Mole) Control 
NDC: 51393-6668 | Form: SOLUTION/ DROPS
Manufacturer: Forces of Nature
Category: homeopathic | Type: HUMAN OTC DRUG LABEL
Date: 20110331

ACTIVE INGREDIENTS: CALENDULA OFFICINALIS FLOWERING TOP 8 [hp_X]/1000 mL; Phytolacca Americana Root 8 [hp_X]/1000 mL; Silicon Dioxide 8 [hp_X]/1000 mL; Thuja occidentalis Leafy Twig 8 [hp_X]/1000 mL
INACTIVE INGREDIENTS: Tea Tree Oil; GERANIUM OIL, ALGERIAN TYPE; LAVANDIN OIL; LEMON OIL; Sesame Oil; CITRONELLA OIL; CEDAR LEAF OIL; CLOVE OIL

Mole Control
Extra Strength

Drug Facts

ACTIVE INGREDIENT

PURPOSE

Active Ingredients [The letters 'HPUS' indicate that the component(s) in this product is (are) officially monographed in the Homœopathic Pharmacopœia of the United States.]
Equal parts of: | Purpose
Calendula Officinalis 8X HPUS | Promotes healthy skin and healing
Phytolacca Americana 8X HPUS | Remedy for skin tags, moles and warts
Silicea 8X HPUS | Remedy for boils and pustules, unhealthy skin
Thuja occidentalis 8X HPUS | Remedy for moles and nevi

Also Includes

Certified Organic Oil of: Citronella, Clove, East Indian Lemongrass, Lavandin, Pelargonium Graveolens Leaf, Sesame, Tea Tree, Cedar Leaf, Lemon

Directions

Apply three times a day directly to mole(s) using a cotton swab, or apply directly with fingers and wash hands with warm soap and water. Avoid contact with the eyes. External use only.

Indications

For the treatment of moles (nevi). It can be used to help remove moles occurring anywhere on the body.

Warnings

PREGNANCY OR BREAST FEEDING

As with all medicine, if you are pregnant or breast-feeding, ask a health professional before use.

KEEP OUT OF REACH OF CHILDREN

Keep out of the reach of children. If accidental ingestion occurs more than several drops, get medical help or contact a Poison Control Center.

WHEN USING

For external use only. Keep away from eyes.

Keep out of the reach of children.

Stop use and ask a doctor if condition worsens or symptoms last more than 7 days or clear up and occur again within a few days.

PRINCIPAL DISPLAY PANEL - 11ml Container

FORCES OF NATURE ®

Mole
CONTROL
EXTRA STRENGTH

HOMEOPATHIC
MEDICINE
FDA REGISTERED
+
USDA
ORGANIC

11ml